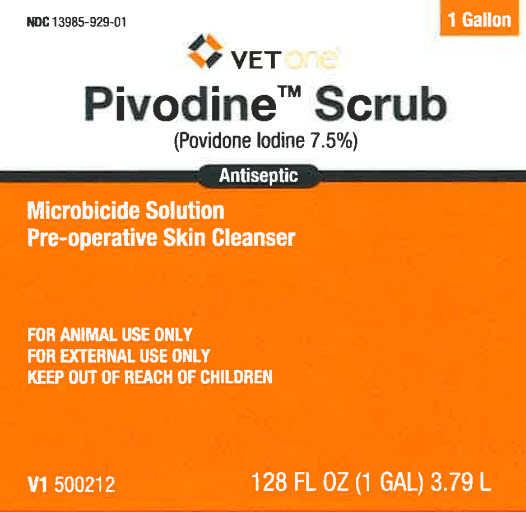 DRUG LABEL: Povidone-Iodine
NDC: 13985-929 | Form: SOLUTION
Manufacturer: MWI/VETONE
Category: animal | Type: OTC ANIMAL DRUG LABEL
Date: 20250317

ACTIVE INGREDIENTS: POVIDONE-IODINE 75 mg/1 mL
INACTIVE INGREDIENTS: ALCOHOL; C12-13 PARETH-9; CITRIC ACID MONOHYDRATE; SODIUM PHOSPHATE, DIBASIC, ANHYDROUS; HYDROXYETHYL CELLULOSE, UNSPECIFIED; SODIUM HYDROXIDE; WATER

Vetone (Vet Drug Listing) 111.000/111AA /485AD
Povidone Iodine Scrub 7.5%

Ingredients

ACTIVE INGREDIENT: Povidone-Iodine 7.5% (0.75% available Iodine)

INACTIVE INGREDIENT: alcohol denat., C12-13 pareth-9. citric acid, disodium phosphate, hydroxyethylcellulose, sodium hydroxide, water

Indications and Use

INDICATIONS: A germicidal cleanser for preoperative and postoperative skin washing, and shampoo for bacterial and fungal skin infections in animals. Used routinely, it helps prevent infection in cuts, scratches, abrasions, and burns. Non-staining to skin, hair and natural fabrics after repeated wash.

DIRECTIONS FOR USE: PREOPERATIVE SKIN PREPARATION: After the surgical area is clipped, wet with water. Apply scrub (1 mL is sufficient to cover an area of 20 to 30 square inches), develop lather, and scrub thoroughly for approximately 5 minutes. Rinse using sterile gauze saturated with water. The area may then be painted with Povidone Iodine Scrub and allowed to dry.

Warning

For external use only. Do not use this product in the eyes or on food-producing animals.

When using this product, prolonged exposure to wet solution may cause irritation or, rarely, severe skin reactions. In preoperative prepping, avoid “pooling” beneath the animal. Stop use and ask a veterinarian if irritation and redness develops or in rare instances of local irritation or sensitivity. If swallowed, get medical help or contact a Poison Control Center right away.

Storage

Store at controlled room temperature between 15° – 30° C (59° – 86° F). Keep container tightly closed when not in use.

Adverse event

TAKE TIME OBSERVE LABEL DIRECTIONS

Distributed by: MWI, Boise, ID 83705

www.VetOne.net

Principal Panel Display

NDC 13985-929-01

VETONE

Pivodine Scrub

(Povidone Iodine 7.5%)

Antiseptic

Microbicide Solution

Pre-operative Skin Cleanser

FOR ANIMAL USE ONLY

FOR EXTERNAL USE ONLY

KEEP OUT OF REACH OF CHILDREN

128 FL OZ (1 GAL) 3.79 L